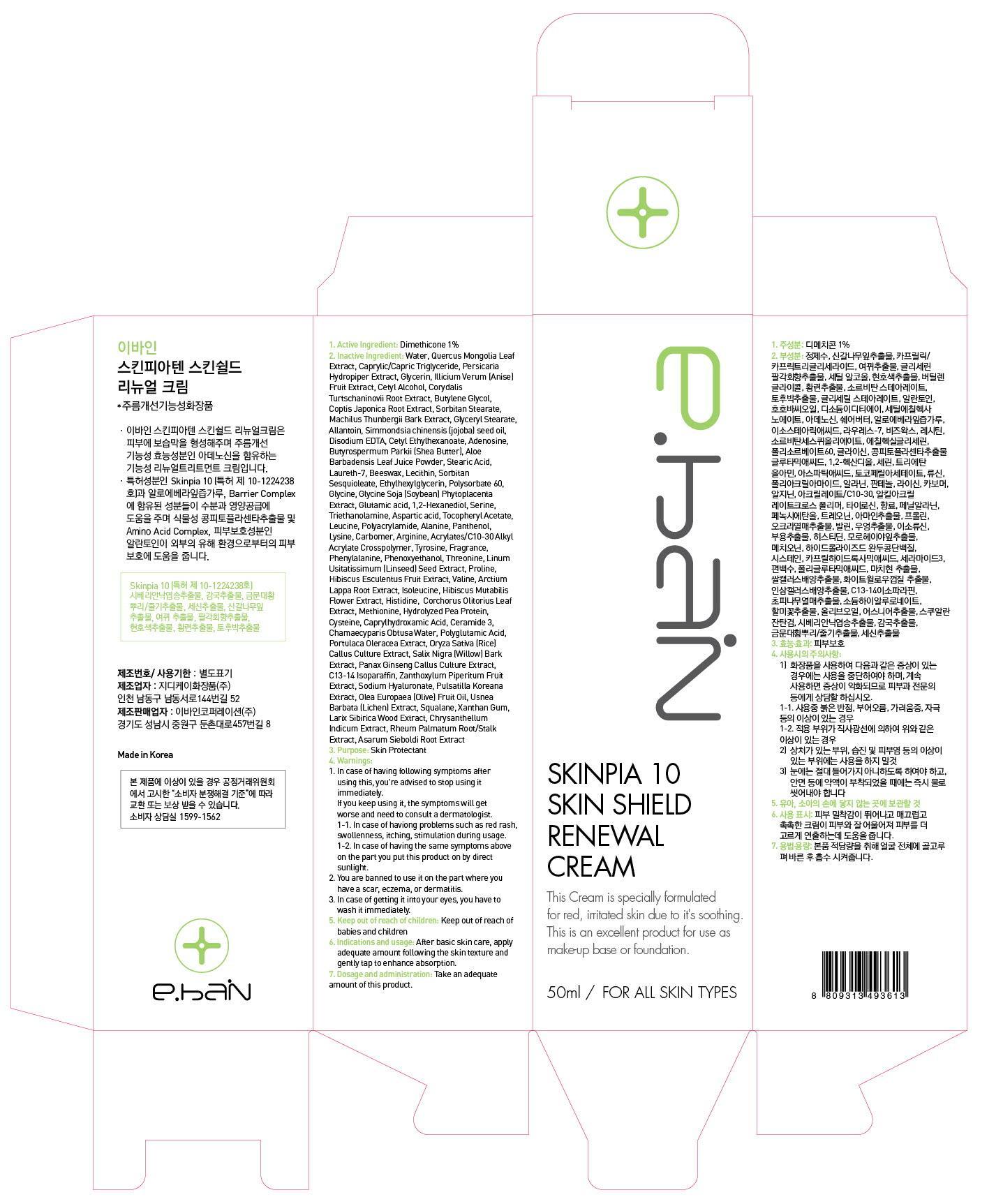 DRUG LABEL: SKINPIA 10 SKIN SHIELD RENEWAL
NDC: 62242-030 | Form: CREAM
Manufacturer: EBAIN Corporation Co., Ltd.
Category: otc | Type: HUMAN OTC DRUG LABEL
Date: 20140304

ACTIVE INGREDIENTS: Dimethicone 0.5 mg/50 mL
INACTIVE INGREDIENTS: Water; Glycerin

ACTIVE INGREDIENT

Active Ingredient: Dimethicone 1%

INACTIVE INGREDIENT

Inactive Ingredients:
Water, Caprylic/Capric Triglyceride, Glycerin, Cetyl Alcohol, Butylene Glycol, Sorbitan Stearate, Glyceryl Stearate, Simmondsia chinensis (jojoba) seed oil, Cetyl Ethylhexanoate, Butyrospermum Parkii (Shea Butter), Stearic Acid, Beeswax, Sorbitan Sesquioleate,
Polysorbate 60, Glycine Soja (Soybean) Phytoplacenta Extract, 1,2-Hexanediol, Triethanolamine, Tocopheryl Acetate, Polyacrylamide, Panthenol, Carbomer, Acrylates/C10-30 Alkyl Acrylate Crosspolymer, Fragrance, Phenoxyethanol, Linum Usitatissimum (Linseed) Seed Extract, Hibiscus Esculentus Fruit Extract, Arctium Lappa Root Extract, Hibiscus Mutabilis Flower Extract, Corchorus Olitorius Leaf Extract, Hydrolyzed Pea Protein, Caprylhydroxamic Acid, Chamaecyparis Obtusa Water, Portulaca Oleracea Extract,
Salix Nigra (Willow) Bark Extract, C13-14 Isoparaffin, Sodium Hyaluronate, Olea Europaea (Olive) Fruit Oil, Squalane, Larix Sibirica Wood Extract, Chrysanthellum Indicum Extract, Rheum Palmatum Root/Stalk Extract, Asarum Sieboldi Root Extract, Quercus Mongolia Leaf Extract, Persicaria Hydropiper Extract, Illicium Verum (Anise) Fruit Extract, Corydalis Turtschaninovii Root Extract, Coptis Japonica Root Extract, Machilus Thunbergii Bark Extract, Allantoin, Disodium EDTA, Adenosine, Aloe Barbadensis Leaf Juice Powder, Laureth-7, Lecithin, Ethylhexylglycerin, Glycine, Glutamic acid, Serine, Aspartic acid, Leucine, Alanine, Lysine, Arginine, Tyrosine, Phenylalanine, Threonine, Proline, Valine, Isoleucine, Histidine, Methionine, Cysteine, Ceramide 3, Polyglutamic Acid, Oryza Sativa (Rice) Callus Culture Extract, Panax Ginseng Callus Culture Extract, Zanthoxylum Piperitum Fruit Extract, Pulsatilla Koreana Extract, Usnea Barbata (Lichen) Extract,
Xanthan Gum

PURPOSE

Purpose: Skin Protectant

WARNINGS

1. In case of having following symptoms after using this, you're advised to stop using it immediately.
If you keep using it, the symptoms will get worse and need to consult a dermatologist.
- In case of haviong problems such as red rash, swollenness, itching, stimulation during usage.
- In case of having the same symptoms above on the part you put this product on by direct sunlight.
2. You are banned to use it on the part where you have a scar, eczema, or dermatitis.
3. In case of getting it into your eyes, you have to wash it immediately.

Keep out of reach of children: Keep out of reach of babies and children

Indications and usage: After basic skin care, apply adequate amount following the skin texture and gently tap to enhance absorption.

Dosage and administration: Take an adequate amount of this product.